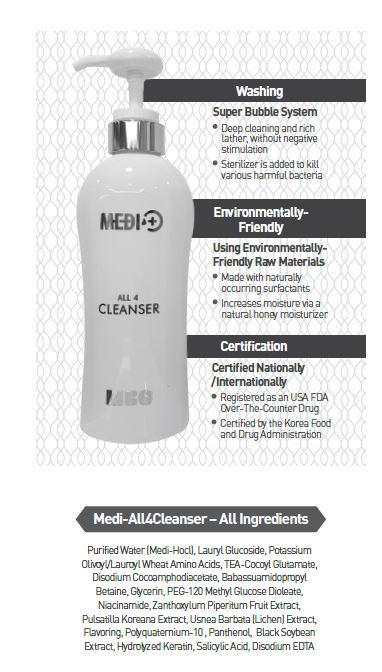 DRUG LABEL: CLAON ALL 4 CLEANSER
NDC: 70694-0002 | Form: LIQUID
Manufacturer: Inc MBG
Category: otc | Type: HUMAN OTC DRUG LABEL
Date: 20190124

ACTIVE INGREDIENTS: LAURYL GLUCOSIDE 16.5 g/100 mL
INACTIVE INGREDIENTS: WATER

INDICATIONS AND USAGE

Hair
After soaking hair with warm water, pour a moderate amount onto the hands, gently massage the product onto the scalp and hair, and then wash out the product thoroughly.
Shaving
With warm water, wet the area that will be shaved, pour a moderate amount and create a foam, shave, and then wash out the product thoroughly.
Body
Take a moderate amount of product and put onto a shower puff or sponge, massage the entire body, and then wash out the product thoroughly.
Foam Cleanser
Wet the entire face, pour a moderate amount and create a foam, gently massage the face and then wash out the product thoroughly with warm water

Keep out of reach of children.

DOSAGE AND ADMINISTRATION

for external use only

WARNINGS

Any cosmetics displaying abnormalities must stop being used, and continual use may lead to worsening symptoms and consultation of a physician.
- Red spots, swelling, itching, stimulations, or other symptoms.
- Any applied area that becomes adversely affected by sunlight.

PURPOSE

Deep cleaning and rich lather, without negative stimulation

Sterilizer is added to kill various harmful bacteria

INACTIVE INGREDIENT

Purified Water (Medi-Hocl), Potassium Olivoyl/Lauroyl Wheat Amino Acids, TEA-Cocoyl Glutamate, Disodium Cocoamphodiacetate, Babassuamidopropyl Betaine, Glycerin, PEG-120 Methyl Glucose Dioleate, Niacinamide, Zanthoxylum Piperitum Fruit Extract, Pulsatilla Koreana Extract, Usnea Barbata (Lichen) Extract, Flavoring, Polyquaternium-10 , Panthenol, Black Soybean Extract, Hydrolyzed Keratin, Salicylic Acid, Disodium EDTA

ACTIVE INGREDIENT

Lauryl Glucoside